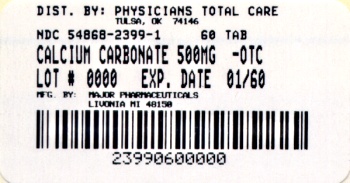 DRUG LABEL: Calcium Carbonate
NDC: 54868-2399 | Form: TABLET, CHEWABLE
Manufacturer: Physicians Total Care, Inc.
Category: otc | Type: HUMAN OTC DRUG LABEL
Date: 20120524

ACTIVE INGREDIENTS: CALCIUM CARBONATE 500 mg/1 1
INACTIVE INGREDIENTS: ADIPIC ACID; DEXTROSE; MALTODEXTRIN; MINERAL OIL; POLYETHYLENE GLYCOLS; POWDERED CELLULOSE; TALC

Active ingredient (in each tablet)

Calcium carbonate USP 500mg

Purpose

Antacid

Uses

relieves

- heartburn
- sour stomach
- acid indigestion
- upset stomach associated with these symptoms

Warnings

Ask a doctor before use if you have

- kidney stones
- a calcium-restricted diet

Ask a doctor or pharmacist before use if you are

- now taking a prescription drug. Antacids may interact with certain prescription drugs.

When using this product

- do not take more than 15 tablets in 24 hours
- do not use the maximum dosage for more than 2 weeks

Directions

- chew 2 - 4 tablets as symptoms occur, or as directed by a doctor

Other information

- each tablet contains: calcium 215 mg and magnesium 5 mg
- store at 20-25°C (68-77°F)

Inactive ingredients

adipic acid, blue #1 aluminum lake, dextrose, flavors, maltodextrin, mineral oil, polyethylene glycol, powdered cellulose, red #40 aluminum lake, talc, yellow #5 aluminum lake (tartrazine), yellow #6 aluminum lake

Questions?

1-800-616-2471

Principal Display Panel

CALCIUM
Antacid Tablets
Regular Strength
ANTACID/CALCIUM SUPPLEMENT
Calcium Carbonate 500 mg
Assorted Fruit
Naturally & Artificially Flavored

Bottles of 60 | NDC 54868-2399-1